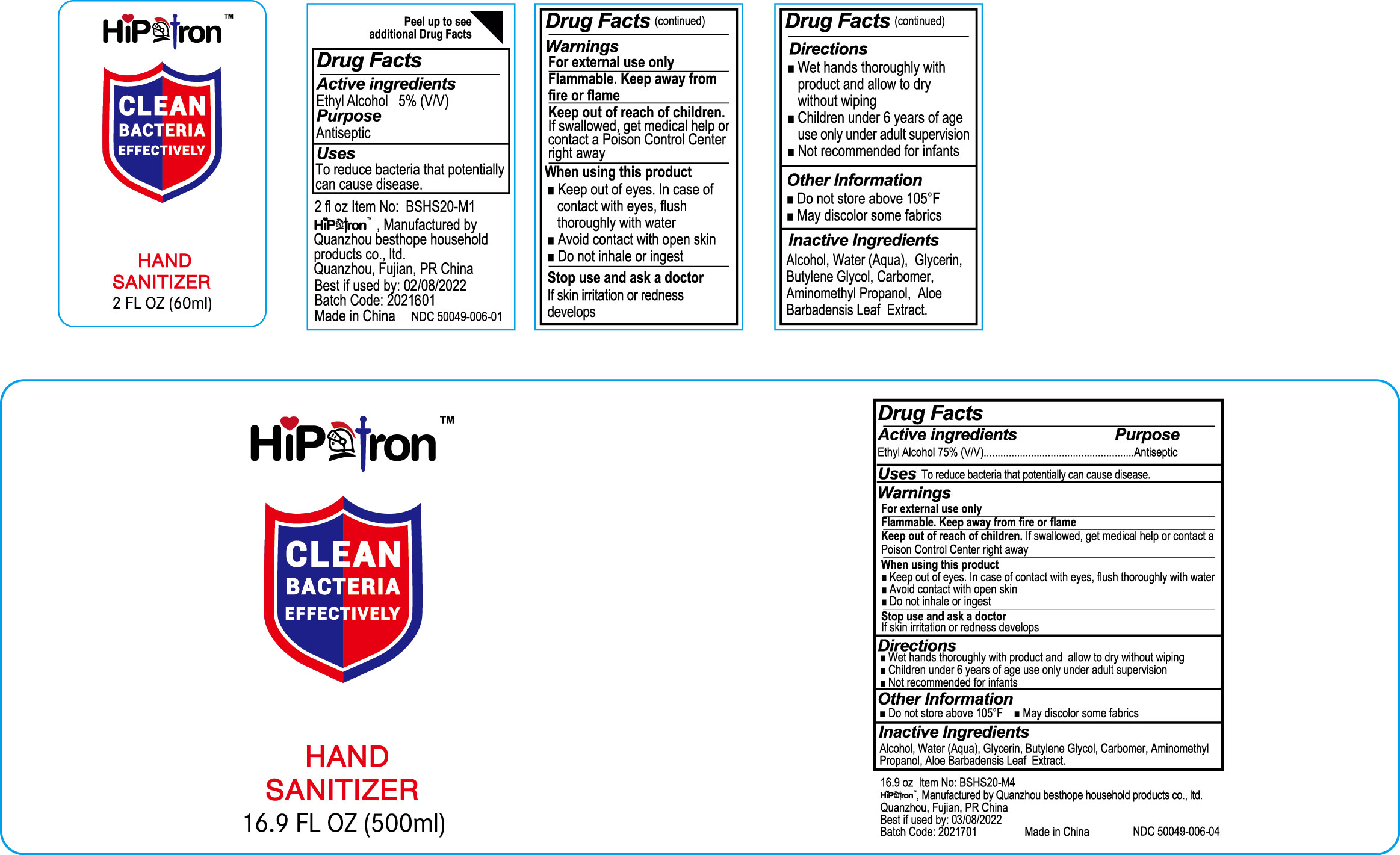 DRUG LABEL: hand sanitizer
NDC: 50049-006 | Form: GEL
Manufacturer: QUANZHOU BESTHOPE HOUSEHOLD PRODUCTS CO.,LTD.
Category: otc | Type: HUMAN OTC DRUG LABEL
Date: 20200820

ACTIVE INGREDIENTS: ALCOHOL 75 mL/100 mL
INACTIVE INGREDIENTS: CARBOMER HOMOPOLYMER, UNSPECIFIED TYPE; AMINOMETHYLPROPANOL; WATER; GLYCERIN; ALOE VERA LEAF; BUTYLENE GLYCOL

50049-006 75%Alcohol Hand Sanitizer

Active Ingredient

Ethyl Alcohol 75%

Purpose

Antiseptic

Use

Use To reduce bacteria that potentially
Can cause disease.

WARNINGS

Warnings For external use only. Flammable. Keep away from
heat and flame. Keep out of reach of children. If swallowed, get
medical help or contact a Poison Control Center right away
When using this product
1 Keep out of eyes. In case of contact with eyes, flush thoroughly with water
■Avoid contact with open skin ■ Do not inhale or ingest
Stop use and ask a doctor if skin irritation or redness develops

Keep out of reach of children. If swallowed, get
medical help or contact a Poison Control Center right away

Directions

Wet hands thoroughly with product and allow to dry without wiping
Children under 6 years of age use only under adult supervision
Not recommended for infants

Inactive ingredients

Alcohol, Water (Aqua), Glycerin, Butylene Glyool, Carbomer, Aminomethyl
Propanol, Aloe Barbadensis Leaf Extract.